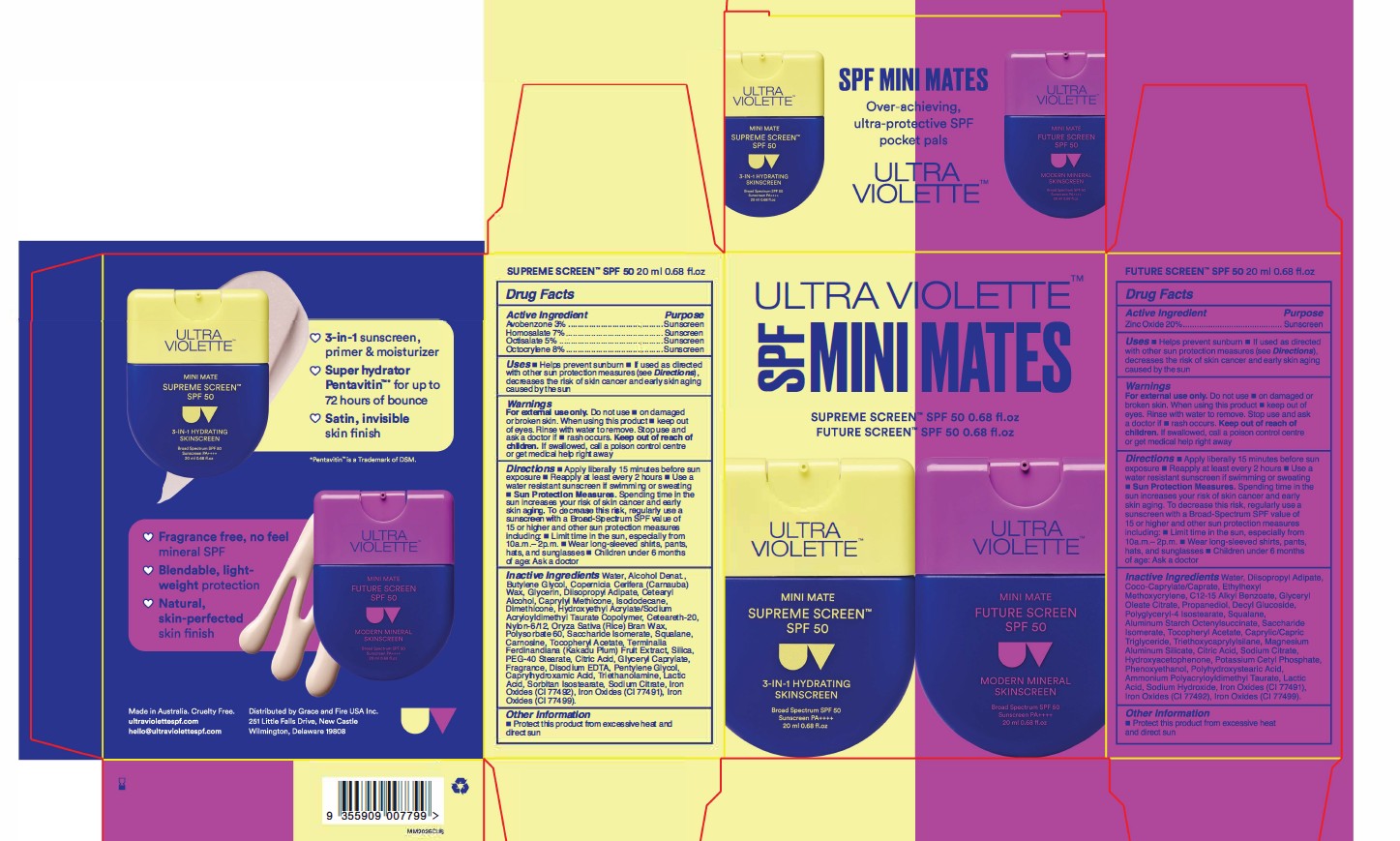 DRUG LABEL: Ultra Violette SPF Mini Mates Duo Pocket Pals
NDC: 84803-112 | Form: LOTION
Manufacturer: Grace and Fire USA Inc.
Category: otc | Type: HUMAN OTC DRUG LABEL
Date: 20260119

ACTIVE INGREDIENTS: AVOBENZONE 30 mg/1 mL; HOMOSALATE 70 mg/1 mL; OCTOCRYLENE 80 mg/1 mL; ZINC OXIDE 200 mg/1 mL; OCTISALATE 50 mg/1 mL
INACTIVE INGREDIENTS: SODIUM CITRATE; CAPRYLYL TRISILOXANE; ALCOHOL; DIISOPROPYL ADIPATE; GLYCERIN; PROPANEDIOL; POLYGLYCERYL-4 ISOSTEARATE; TRIETHANOLAMINE; CARNOSINE; .ALPHA.-TOCOPHEROL ACETATE; POLYHYDROXYSTEARIC ACID (2300 MW); CETEARETH-20; COCO-CAPRYLATE/CAPRATE; TRIETHOXYCAPRYLYLSILANE; POLYSORBATE 60; KAKADU PLUM; CAPRYLIC/CAPRIC TRIGLYCERIDE; BUTYLENE GLYCOL; HYDROXYACETOPHENONE; SORBITAN ISOSTEARATE; GLYCERYL OLEATE CITRATE; DECYL GLUCOSIDE; ALUMINUM STARCH OCTENYLSUCCINATE; AMMONIUM POLYACRYLOYLDIMETHYL TAURATE; HYDROXYETHYL ACRYLATE/SODIUM ACRYLOYLDIMETHYL TAURATE COPOLYMER (100000 MPA.S AT 1.5%); CAPRYLHYDROXAMIC ACID; GLYCERYL CAPRYLATE; SILICON DIOXIDE; SACCHARIDE ISOMERATE; ISODODECANE; CETOSTEARYL ALCOHOL; WATER; ETHYLHEXYL METHOXYCRYLENE; CI 77491; DIMETHICONE; MAGNESIUM ALUMINUM SILICATE; CITRIC ACID; SODIUM HYDROXIDE; NYLON-12; EDETATE DISODIUM; LACTIC ACID; CARNAUBA WAX; RICE BRAN; CI 77492; CI 77499; PENTYLENE GLYCOL; C12-15 ALKYL BENZOATE; POTASSIUM CETYL PHOSPHATE; PHENOXYETHANOL; SQUALANE; PEG-40 STEARATE

Ultra Violette SPF Mini Mates Duo Pocket Pals Contains
1 X Supreme Screen SPF50 20ml NDC 84803-100-21
1 X Future Screen SPF50 20ml NDC 84803-103-21

ACTIVE INGRDIENTS : SUPREME SCREEN SPF 50

AVOBENZONE 3.0%
HOMOSALATE 7.0%
OCTISALATE 5.0%
OCTOCRYLENE 8.0%

ACTIVE INGREDIENTS: FUTURE SCREEN SPF 50

ZINC OXIDE 20%

PURPOSE

SUNSCREEN

INDICATIONS AND USAGE

HELPS PREVENT SUNBURN

If used as directed with other sun protection measures (see Directions), decreases the risk of skin cancer and early skin aging caused by the sun

WARNINGS

.

FOR EXTERNAL USE ONLY

DO NOT USE

ON DAMAGED OR BROKEN SKIN

WHEN USING

KEEP OUT OF EYES. RINSE WITH WATER TO REMOVE

STOP USE AND ASK A DOCTOR IF

RASH OCCURS

KEEP OUT OF REACH OF CHILDREN

IF SWALLOWED, GET MEDICAL HELP OR CONTACT A POISON CONTROL CENTER RIGHT AWAY

DIRECTIONS

Directions for Sunscreen Use

- apply liberally and evenly 15 minutes before sun exposure
- reapply at least every 2 hours
- use a water resistant sunscreen if swimming or sweating
- Sun Protection Measures. Spending time in the sun increases your risk of skin cancer and early skin aging. To decrease this risk, regularly use a sunscreen with a Broad Spectrum SPF value of 15 or higher and other sun protection measures including:
  - limit time in the sun, especially from 10 a.m. – 2 p.m.
- wear long-sleeved shirts, pants, hats, and sunglasses
- children under 6 months of age: Ask a doctor

INACTIVE INGREDIENTS

SUPREME INACTIVE INGREDIENTS : Water, Alcohol Denat., Butylene Inactive Glycol, Copernicia Cerifera (Carnauba) Wax, Glycerin, Diisopropyl Adipate, Cetearyl Alcohol, Caprylyl Methicone, lsododecane, Dimethicone, Hydroxyethyl Acrylate/Sodium Acryloyldimethyl Taurate Copolymer, Ceteareth-20, Nylon-6/12, Oryza Sativa (Rice) Bran Wax, Polysorbate 60, Saccharide lsomerate, Squalane, Carnosine, Tocopheryl Acetate, Terminalia Ferdinandiana (Kakadu Plum) Fruit Extract, Silica, PEG-40 Stearate, Citric Acid, Glyceryl Caprylate, Fragrance, Disodium EDTA, Pentylene Glycol, Caprylhydroxamic Acid, Triethanolamine, Lactic Acid, Sorbitan lsostearate, Sodium Citrate, Iron Oxides (Cl 77492), Iron Oxides (Cl 77491), Iron Oxides (Cl 77499).

FUTURE INACTIVE INGREDIENTS: Water, Diisopropyl Adipate, Coco-Caprylate/Caprate, Ethylhexyl Methoxycrylene, C12-15 Alkyl Benzoate, Glyceryl Oleate Citrate, Propanediol, Decyl Glucoside, Polyglyceryl-4 Isostearate, Squalane, Aluminum Starch Octenylsuccinate, Saccharide Isomerate, Tocopheryl Acetate, Caprylic/Capric Triglyceride, Triethoxycaprylylsilane, Magnesium Aluminum Silicate, Citric Acid, Sodium Citrate, Hydroxyacetophenone, Potassium Cetyl Phosphate, Phenoxyethanol, Polyhydroxystearic Acid, Ammonium Polyacryloyldimethyl Taurate, Lactic Acid, Sodium Hydroxide, Iron Oxides (CI 77491), Iron Oxides (CI 77492), Iron Oxides (CI 77499).

Other Information

Protect this product from excessive heat and direct sun

PACKAGE LABEL

Ultra Violette SPF Mini Mates Duo Pocket Pals Contains
1 X Supreme Screen SPF50 20 ml 0.68 fl. oz NDC 84803-100-21
1 X Future Screen SPF50 20 ml 0.68 fl. oz NDC 84803-103-21